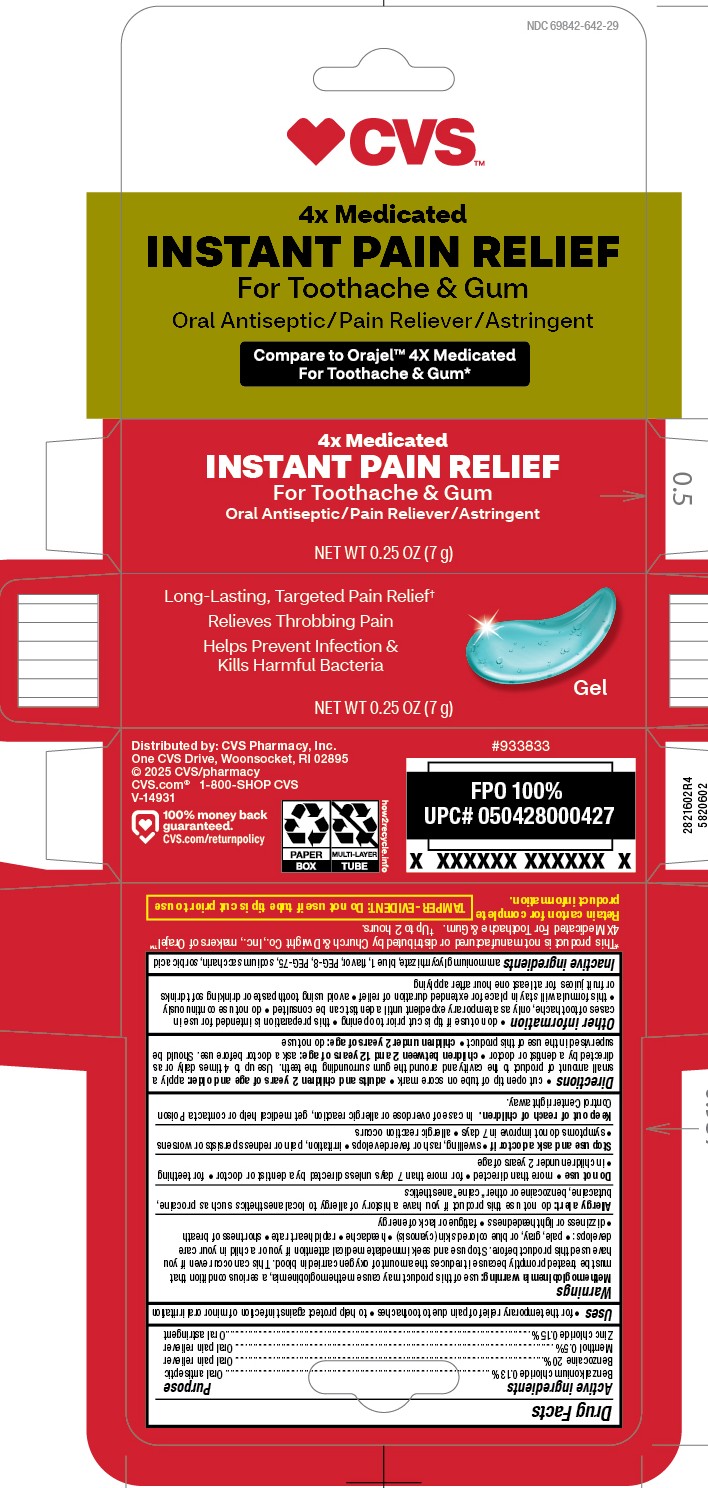 DRUG LABEL: 4x Medicated Toothache and Gum Gel
NDC: 69842-642 | Form: GEL
Manufacturer: CVS
Category: otc | Type: HUMAN OTC DRUG LABEL
Date: 20251121

ACTIVE INGREDIENTS: BENZALKONIUM CHLORIDE 0.13 g/100 g; BENZOCAINE 20 g/100 g; MENTHOL, UNSPECIFIED FORM 0.5 g/100 g; ZINC CHLORIDE 0.15 g/100 g
INACTIVE INGREDIENTS: POLYETHYLENE GLYCOL 400; AMMONIUM GLYCYRRHIZATE; POLYETHYLENE GLYCOL 3350; SACCHARIN SODIUM; METHYL SALICYLATE; FD&C BLUE NO. 1; SORBIC ACID

5820602 4x Medicated Instant Pain Relief Gel

ACTIVE INGREDIENT

Benzalkonium chloride 0.13% . . . Oral antiseptic

Benzocaine 20% . . . Oral pain reliever

Menthol 0.5% . . . Oral pain reliever

Zinc chloride 0.15% . . . Oral astringent

PURPOSE

Use

for the temporary relief of pain due to toothaches * to help protect against infection of minor oral irritation

WARNINGS

Methemoglobinema warning: use of this product may cause methemoglobinemia, a serious condition that must be treated promptly becuase it reduces the amount of oxygen carried in blood. This can occur even if you have used this product before. Stop use and seek immediate medical attention if you or a child in your care develops: * pale, gray, or blue colored skin (cyanosis) * headache * rapid heart rate * shortness of breath * dizziness or lightheadedness * fatigue or lack of energy

Allergy alert: do not use this product if you have a history of allergy to local anesthetics such as procaine, butacaine, benzocaine or other "caine" anesthetics

Do not use * more than directed * for more than 7 days unless told to do so by a dentist or doctor * for teething * in children under 2 years of age

Stop use and ask a doctor if * swelling, rash or fever develops * irritation, pain or redness persists or worsens * symptoms do not imporve in 7 days * allergic reaction occurs

Keep out of reach of children. In case of overdose, get medical help or contact a Poison Control Center right away.

Directions

cut open tip of tube on score mark * dults and children 2 years of age and older: apply a small amount of product to the cavity and around teh gum surrounding the teeth. Use up to 4 times daily or as directed by a dentist or doctor * children under 12 years of age should be supervised in the use of this product * children under 2 years of age: do not use

Other information

do not use if tip is cut prior to opening * this preparation is intended for use in cases of toothache, only as a temporary expedient until a dentist can be consulted * do not use continuously * this formula will stay in place for extended duration of relief * avoid using toothpaste or drinking soft drinks or fruit juices for least one hour after applying

INACTIVE INGREDIENT

ammonium glycyrrhizate, blue 1, flavor, PEG-8, PEG-75, sodium saccharin, sorbic acid